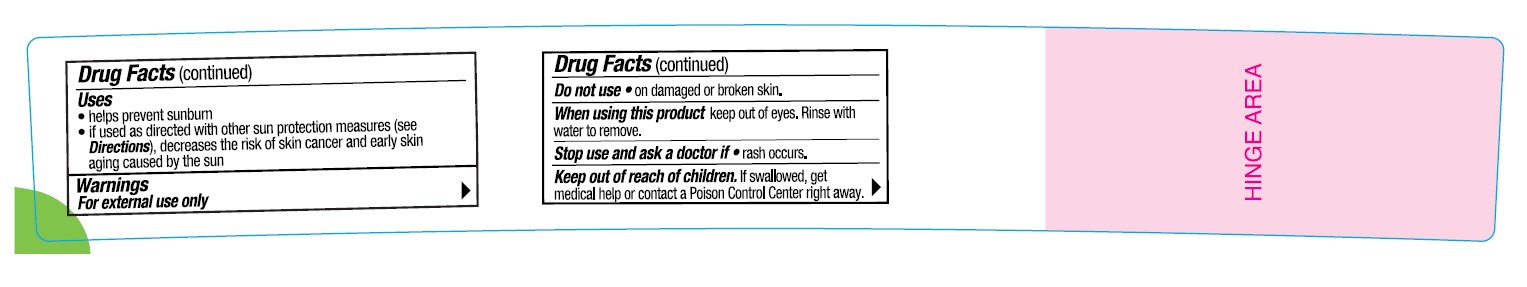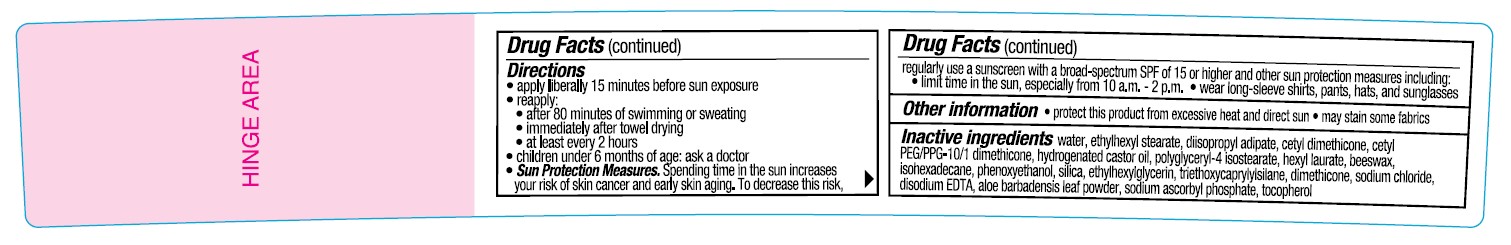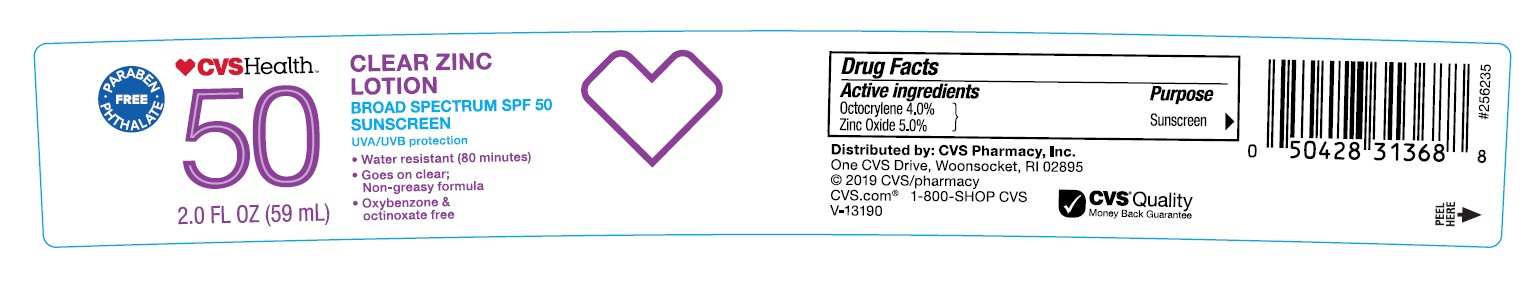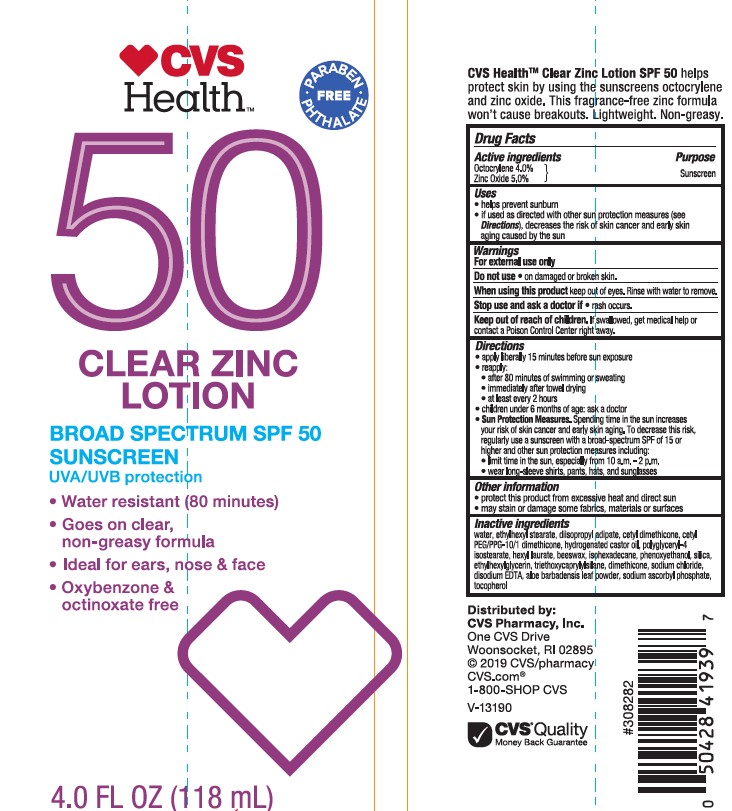 DRUG LABEL: CVS Health 50 Clear Zinc Broad Spectrum SPF 50 Sunscreen
NDC: 51316-043 | Form: LOTION
Manufacturer: CVS PHARMACY
Category: otc | Type: HUMAN OTC DRUG LABEL
Date: 20241017

ACTIVE INGREDIENTS: ZINC OXIDE 50 mg/1 mL; OCTOCRYLENE 40 mg/1 mL
INACTIVE INGREDIENTS: ALOE VERA LEAF; SODIUM CHLORIDE; ETHYLHEXYL STEARATE; WHITE WAX; DIISOPROPYL ADIPATE; HEXAMETHYLDISILOXANE; CETYL DIMETHICONE 45; CETYL PEG/PPG-10/1 DIMETHICONE (HLB 2); ETHYLHEXYLGLYCERIN; HEXYL LAURATE; HYDROGENATED CASTOR OIL; ISOHEXADECANE; POLYGLYCERYL-4 ISOSTEARATE; SILICON DIOXIDE; SODIUM ASCORBYL PHOSPHATE; .ALPHA.-TOCOPHEROL, DL-; PHENOXYETHANOL; TRIETHOXYCAPRYLYLSILANE; WATER; EDETATE DISODIUM

CVS Health 50 Clear Zinc Lotion Broad Spectrum SPF 50 Sunscreen

Active ingredients

Octocrylene 4.0%, Zinc Oxide 5.0%

Purpose

Sunscreen

Uses

- helps prevent sunburn
- if used as directed with other sun protection measures (see Directions), decreases the risk of skin cancer and early skin aging caused by the sun

Warnings

For external use only

Do not use

• on damaged or broken skin.

When using this product

• keep out of eyes. Rinse with water to remove.

Stop use and ask a doctor if

• rash occurs.

Keep out of reach of children.

If swallowed, get medical help or contact a Poison Control Center right away.

Directions

- apply liberally 15 minutes before sun exposure
- use a water resistant sunscreen if swimming or sweating
- reapply at least every 2 hours
- children under 6 months of age: Ask a doctor
- Sun Protection Measures. Spending time in the sun increases your risk of skin cancer and early skin aging. To decrease this risk, regularly use a sunscreen with a Broad Spectrum SPF value of 15 or higher and other sun protection measures including:

• limit time in the sun, especially from 10 a.m. - 2 p.m.

• wear long-sleeved shirts, pants, hats, and sunglasses

Other information

- protect the product in this container from excessive heat and direct sun
- may stain or damage some fabrics, materials or surfaces

Inactive ingredients

WATER, ETHYLHEXYL STEARATE, DIISOPROPYL ADIPATE, CETY DIMETHICONE, CETY PEG/PPG-10/1 DIMETHICONE, HYDROGENATED CASTOR OIL, POLYGLYCERYL-4 ISOSTEARATE, HEXYL LAURATE, BEESWAX, ISOHEXADECANE, PHENOXYETHANOL, SILICA, ETHYLHEXYLGLYCERIN, TRIETHOXYCAPRYLYLSILANE, DIMETHICONE, SODIUM CHLORIDE, DISODIUM EDTA, ALOE BARBADENSIS LEAF POWDER, SODIUM ASCORBYL PHOSPHATE, TOCOPHEROL,